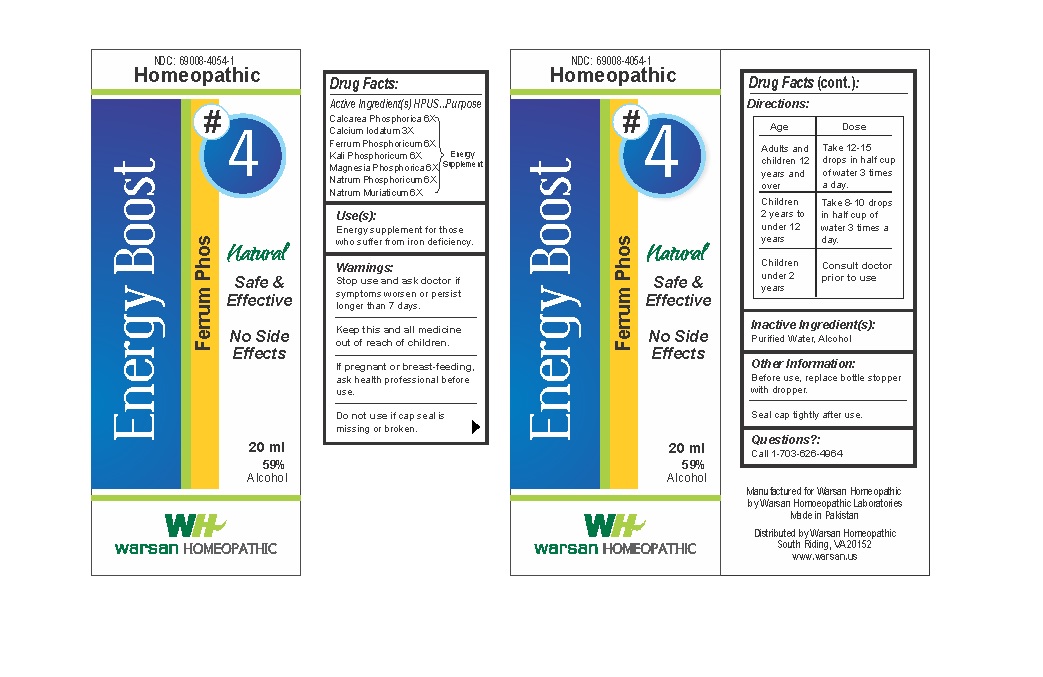 DRUG LABEL: Combination Remedy 4 - Energy Boost
NDC: 69008-4054 | Form: SOLUTION/ DROPS
Manufacturer: Warsan Homoeopathic Laboratories
Category: homeopathic | Type: HUMAN OTC DRUG LABEL
Date: 20171225

ACTIVE INGREDIENTS: TRIBASIC CALCIUM PHOSPHATE 6 [hp_X]/1 mL; CALCIUM IODIDE 3 [hp_X]/1 mL; SODIUM PHOSPHATE, DIBASIC, HEPTAHYDRATE 6 [hp_X]/1 mL; SODIUM CHLORIDE 6 [hp_X]/1 mL; FERRUM PHOSPHORICUM 6 [hp_X]/1 mL; POTASSIUM PHOSPHATE, DIBASIC, TRIHYDRATE 6 [hp_X]/1 mL; MAGNESIUM PHOSPHATE, DIBASIC TRIHYDRATE 6 [hp_X]/1 mL
INACTIVE INGREDIENTS: ALCOHOL; WATER

Stop use and ask doctor if symptoms worsen or persist longer than 7 days.

If pregnant or breast-feeding, ask health professional before use.

Do not use if tamper evident seal is missing or broken.

Keep out of reach of children.

ACTIVE INGREDIENT

Calcarea Phosphorica 6X
Calcium Iodatum 3X
Ferrum Phosphoricum 6X
Kali Phosphoricum 6X
Magnesia Phosphorica 6X
Natrum Phosphoricum 6X
Natrum Muriaticum 6X

PURPOSE

Energy supplement for those who suffer from iron deficiency.

INACTIVE INGREDIENT

Purified Water

Alcohol

DOSAGE AND ADMINISTRATION

Adults and children 12 years and older: Four tablets every thirty minutes for six doses followed by four tablets every 4-6 hours as needed.

Children 2 years to under 12 years: Four tablets every thirty minutes for six doses followed by two tablets every 4-6 hours as needed.

Children under 2 years age: Consult doctor prior to use.

INDICATIONS AND USAGE

Energy supplement for those who suffer from iron deficiency.